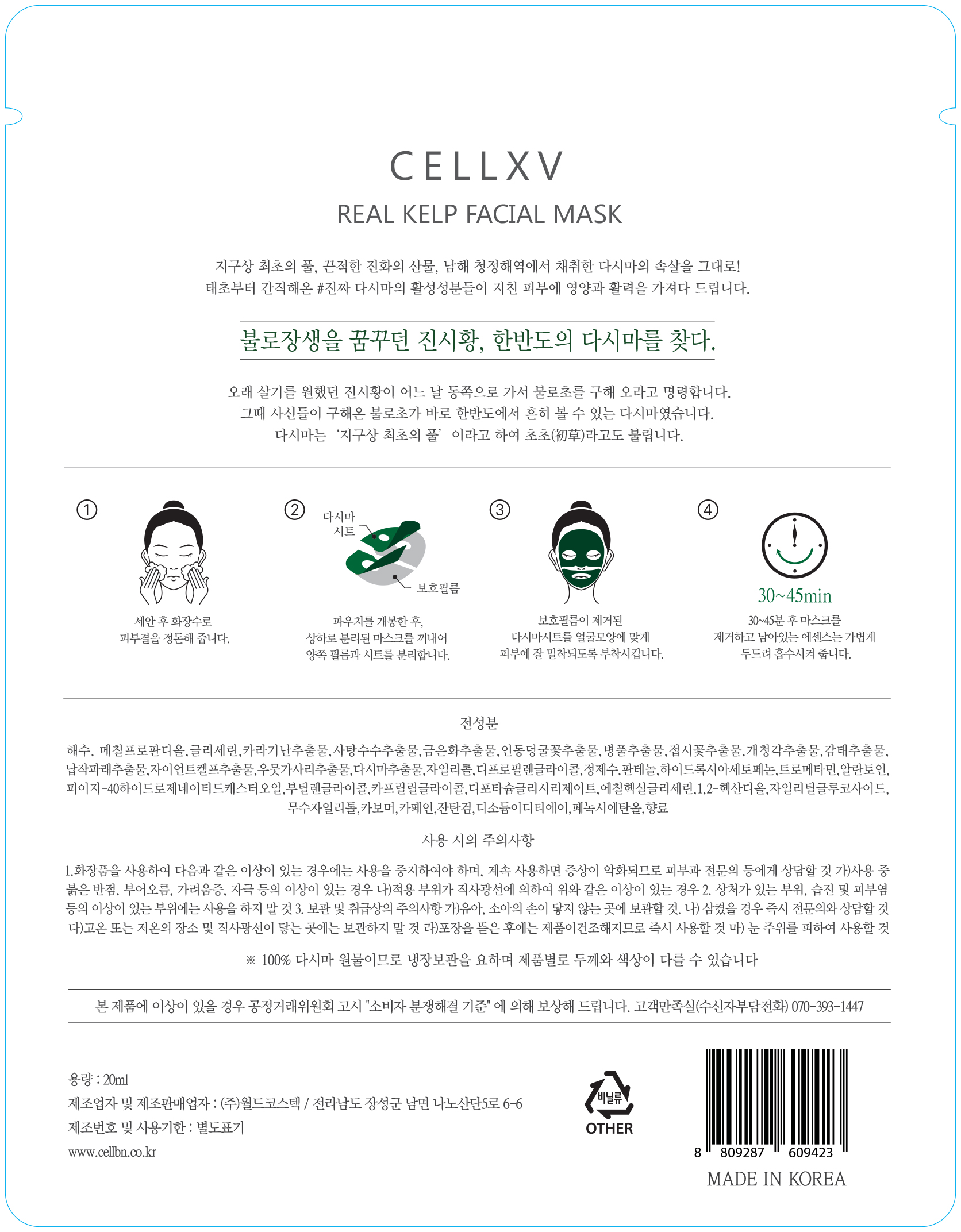 DRUG LABEL: CELLXV REAL KELP FACIAL MASK
NDC: 71450-0010 | Form: LIQUID
Manufacturer: WORLDCOSTEC.CO.,LTD
Category: otc | Type: HUMAN OTC DRUG LABEL
Date: 20170529

ACTIVE INGREDIENTS: ADENOSINE 0.03 g/100 mL; ARBUTIN 1 g/100 mL
INACTIVE INGREDIENTS: WATER; BUTYLENE GLYCOL

ACTIVE INGREDIENT

Arbutin, Adenosine

INACTIVE INGREDIENT

Water, Butylene Glycol, Etc

PURPOSE

Skin Protectant

Keep out of reach of the children

INDICATIONS AND USAGE

Wash and dry your face thoroughly. Remove both sides of film and place upper and lower masks onto face. Leave on for 25~45min. Then remove masks and gently massage your face until the essence is fully absorbed.

WARNINGS

1. If the following symptoms occur after product use, stop using the product immediately and consult a dermatologist (continuous use can exacerbate the symptoms).
1) Occurrence of red spots, swelling, itchiness, and other skin irritation
2) If the symptoms above occur after the application area is exposed to direct sunlight

2. Do not use on open wounds, eczema, and other skin irritations

3. Precaution for Storage and Handling
1) Close the lid after use
2) Keep out of reach of infants and children
3) Do not to store in a place with high/low temperature and exposed to direct sunlight

4. Use as avoiding eye areas.

DOSAGE AND ADMINISTRATION

for external use only